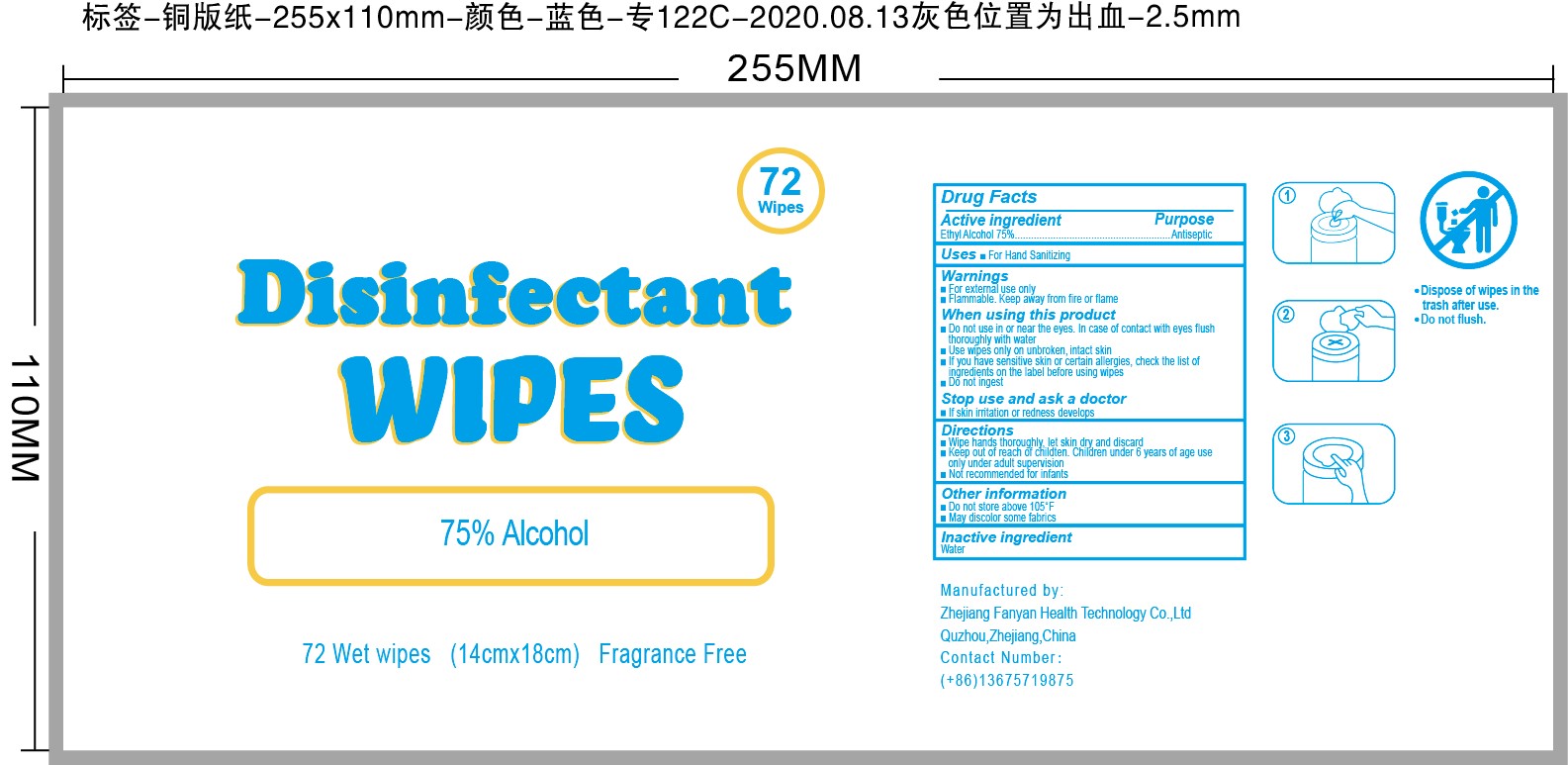 DRUG LABEL: 75% Alcohol Wipes
NDC: 80469-001 | Form: CLOTH
Manufacturer: Zhejiang Fanyan Health Technology Co.,ltd
Category: otc | Type: HUMAN OTC DRUG LABEL
Date: 20201011

ACTIVE INGREDIENTS: ALCOHOL 75 mL/100 g
INACTIVE INGREDIENTS: WATER

75% Alcohol Wipes

Active ingredient

Ethyl Alcohol 75% Antiseptic

Purpose

Antiseptic

Uses

For Hand Sanitizing

Warnings

For external use only

Flammable. Keep away from fire or flame.

When using this product

- Do not use in or near they eyes. In case of contact with eye flush thoroughly with water
- Use wipes only on unbroken, intact skin
- If you have sensitive skin or certain allergies, check the list of ingredients on the label before using wipes
- Do not ingest

Stop use and ask a doctor

If skin irritation or redness develops

Keep out of reach of children. Children under 6 years of age use only under adult supervision

Directions

- Wipe hands thoroughly, let skin dry and discard
- Keep out of reach of children. Children under 6 years of age use only under adult supervision
- Not recommended for infants

Other information

- Do not store above 105F
- May discolor some fabrics

Inactive ingredient

Water

PACKAGE LABEL

80469-001-01 72 PCS

72 Wipes

Disinfectant

WIPES

75% Alcohol

72 Wet wipes (14cm x 18cm) Fragrance free